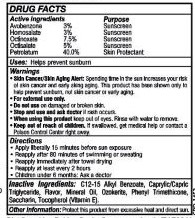 DRUG LABEL: SPF 45 - Lip Balm
NDC: 63645-183 | Form: STICK
Manufacturer: OraLabs
Category: otc | Type: HUMAN OTC DRUG LABEL
Date: 20250422

ACTIVE INGREDIENTS: AVOBENZONE 30 mg/1 g; HOMOSALATE 30 mg/1 g; OCTINOXATE 75 mg/1 g; OCTISALATE 50 mg/1 g; PETROLATUM 400 mg/1 g
INACTIVE INGREDIENTS: LIGHT MINERAL OIL 122 mg/1 g; CERESIN 170 mg/1 g

Drug Facts

Active ingredient

Avobenzone 3.0%, Homosalate 3.0%, Octinoxate 7.5%, Octisalate 5.0%................Sunscreen, Petrolatum 40.0%...........Skin Protectant

Purpose

Sunscreen, Skin Protectant

Keep Out of Reach of Children

If swallowed get medical help or contact a Poison Control Center right away.

Uses

Prevents Sunburns. Helps prevent wind burned and chapped lips.

Warnings

Skin Cancer/Skin Aging Alert: Spending time in the sun increases your risk of skin cancer and early skin aging. This product has been shown to prevent sunburn, skin cancer and/or early aging.

For external use only: Stop use and ask a doctor: if rash or irritation develops and lasts.

Directions

Apply liberally 15 minutes before sun exposure • reapply: after 80 minutes

of swimming or sweating • immediately after towel drying • at least every 2 hours • Sun

Protection Measures.Spending time in the sun increases your risk of skin cancer and

early skin aging • To decrease the risk, regularly use a sunscreen with a broad spectrum

SPF of 15 or higher and other sun protection measures including: limit time in the sun,

especially from 10 a.m. -2 p.m. • wear long-sleeve shirts, pants, hats and sunglasses. Children under 6 months: Ask a doctor.

Inactive Ingredients

C12-15 Alkyl Benzoate, Caprylic/Capric Triglyceride, Mineral Oil, Ozokerite, Phenyl Trimethicone, Tocopherol